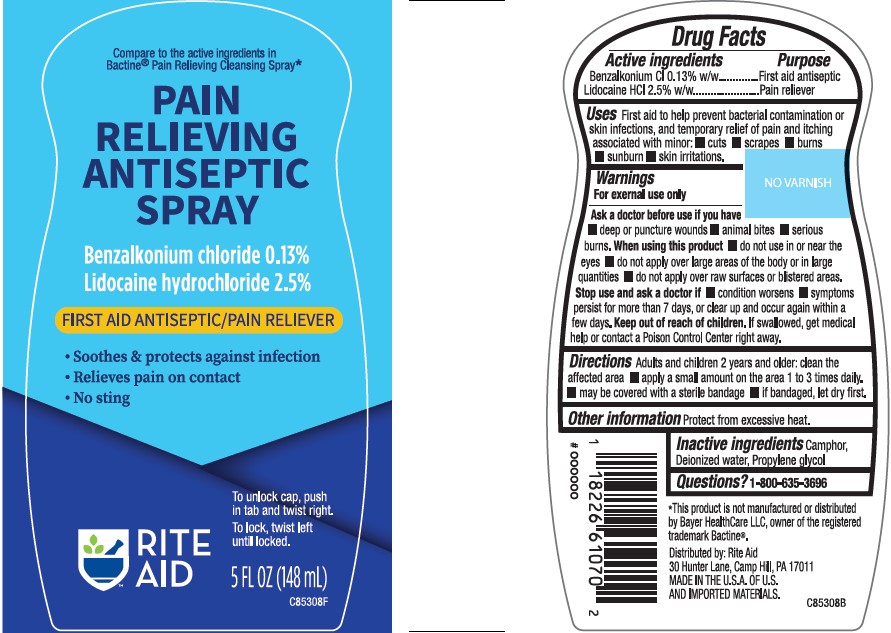 DRUG LABEL: BENZALKONIUM CHLORIDE AND LIDOCAINE HYDROCHLORIDE
NDC: 11822-2001 | Form: LIQUID
Manufacturer: Rite Aid
Category: otc | Type: HUMAN OTC DRUG LABEL
Date: 20220727

ACTIVE INGREDIENTS: BENZALKONIUM CHLORIDE 0.13 g/1 mL; LIDOCAINE 25 mg/1 mL
INACTIVE INGREDIENTS: WATER; PROPYLENE GLYCOL; CAMPHOR (SYNTHETIC)

Rite Aid Pain Relieving Antispetic Spray

PURPOSE

first aid to help prevent skin infection, and for temporary relief of pain

Drug Facts

Active ingredient Purpose

Benzalkonium Cl 0.13% w/w...............................Fist aid Antiseptic
lidocaine HCl 2.5% w/w......................................Pain reliever

Uses

first aid to help prevent bacterial contamination or skin infections, and for temporary relief of pain and itching associated with minor:

■ cuts ■ scrapes ■ burns ■ sunburn ■ skin irritations.

Warnings

For external use only.

Ask a doctor before use if you have

■ deep or puncture wounds

■ animal bites ■ serious burns

When using this product

■ do not use in or near the eyes

■ do not apply over large areas of the body or in large quantities

■ do not apply over raw surfaces or blistered areas.

Stop use and ask a doctor if

■ condition worsens - symptoms

■ persist for more than 7 days, or clear up and occur again within a few days

Keep out of reach of children.

If swallowed, get medical help or contact a Poison Control Center right away.

Directions

■ adults and children 2 years and older: clean the affected area

■ apply a small amount on the area 1 to 3 times daily.

■ may be covered with a sterile bandage

■ if bandaged, let dry first

Other information

Protect from excessive heat.

Inactive ingredients

Camphor, Deionized water, Propylene glycol

Questions?

1-800-635-3696